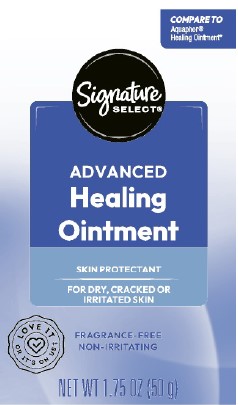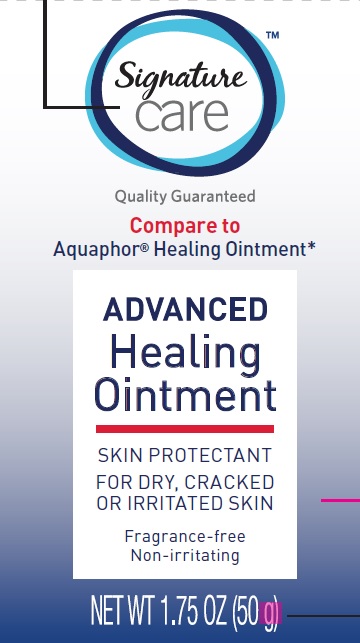 DRUG LABEL: Advanced Healing
NDC: 21130-247 | Form: OINTMENT
Manufacturer: Better Living Brands, LLC
Category: otc | Type: HUMAN OTC DRUG LABEL
Date: 20260223

ACTIVE INGREDIENTS: PETROLATUM 410 mg/1 g
INACTIVE INGREDIENTS: MINERAL OIL; CERESIN; LANOLIN ALCOHOLS; PANTHENOL; GLYCERIN; LEVOMENOL

Signature Care_Signature Select 247.000/247AA-AC
Healing Ointment for Dry and Cracked Skin

Active ingredient

Petrolatum 41%

Purpose

Skin Protectant

Uses

- temporarily protects minor: - cuts - scrapes - burns
- temporarily protects and helps relieve chapped or cracked skin and lips
- helps protect from the drying effects of wind and cold weather

Warnings

For external use only

When using this product

- do not get into eyes

Stop use and ask a doctor if

- condition worsens
- symptoms last more than 7 days or clear up and occur again with in a few days

Keep out of reach of children

If swallowed, get medical help or contact a Poison Control Center right away.

Directions

- apply as needed

inactive ingredients

mineral oil, ceresin, lanolin alcohol, panthenol, glycerin, bisabolol

ADVERSE REACTION

DISTRIBUTED BY BETTER LIVING BRANDS, LLC

P.O. BOX 99, PLEASANTON, CA 94566-0009

‡1-888-723-3929

*This product is not manufactured or distributed by Beiersdorf Inc., distributor of Aquaphor Healing Ointment.

PLASTIC TUBE

how2recycle.info

smartlabel

Scan here for more information

principal display panel

Signature

Care

Quality Guaranteed

COMPARE TO

Aquaphor Healing Ointment*

ADVANCED

Healing

Ointment

Skin Protectant

For dry, cracked or irritated skin

Fragrance-free

Non-irritating

Net Wt 1.75 OZ (50 g)

PRINCIPAL DISPLAY PANEL

COMPARE TO

Aquafor ®

Healing Ointment*

Signature

SELECT ®

ADVANCED

HEALING

OINTMENT

SKIN PROTECTANT

FOR DRY, CRACKED OR IRRITATED SKIN

FRAGRANCE-FREE

NON-IRRITATING

LOVE IT OR IT'S ON US‡

NET WT 1.75 OZ (50 g)